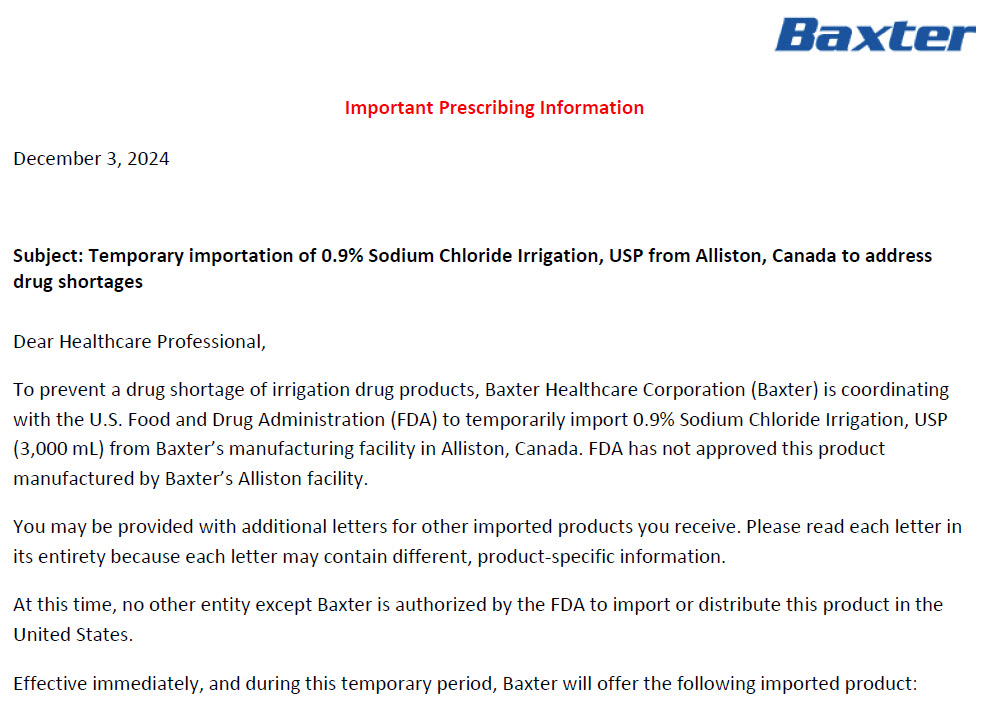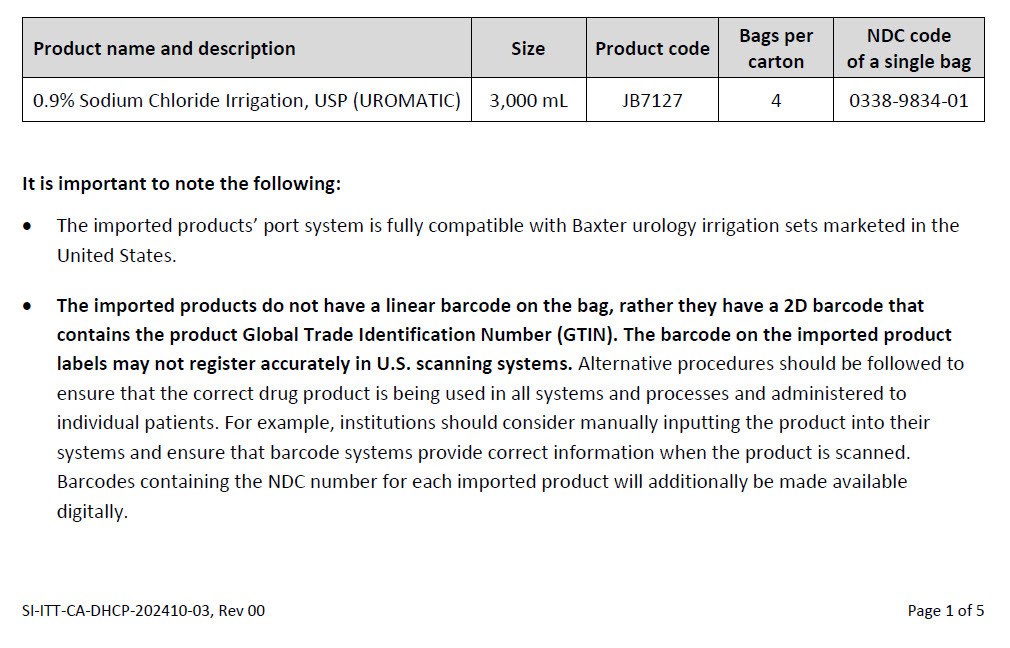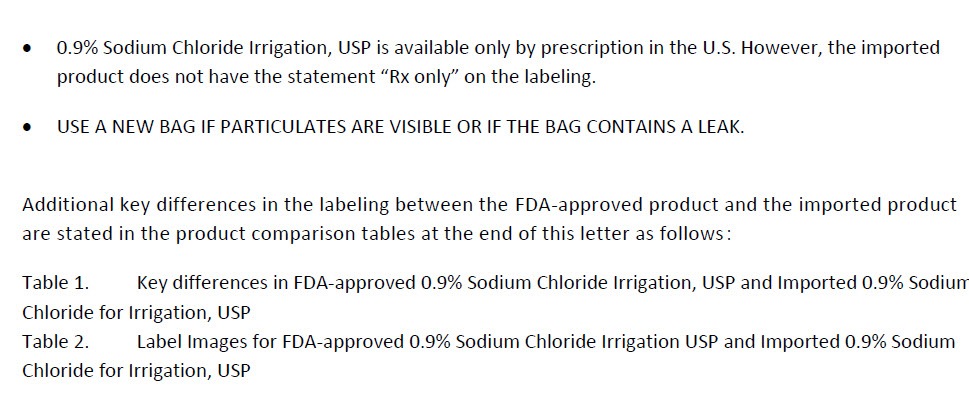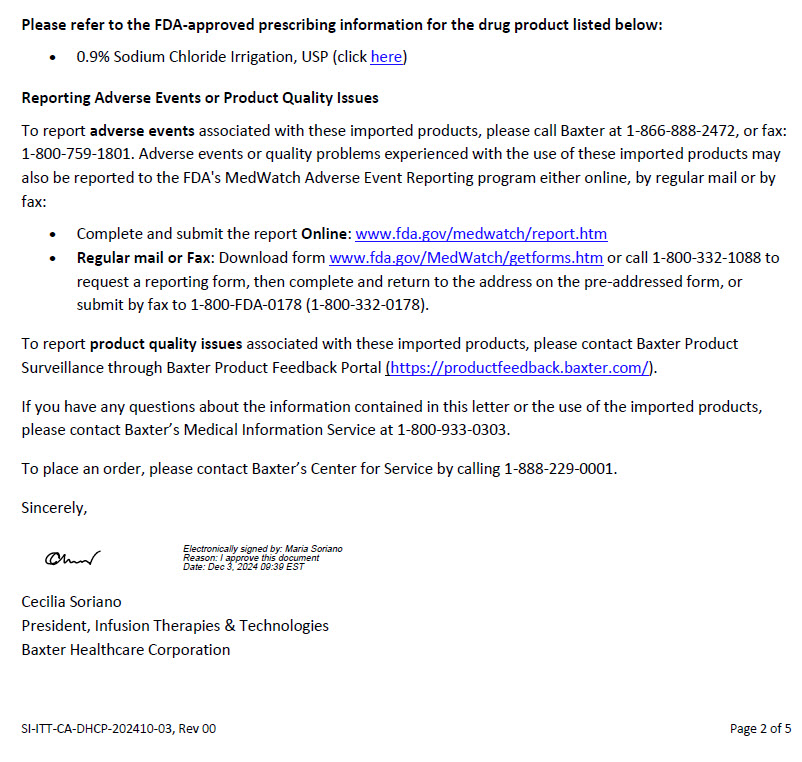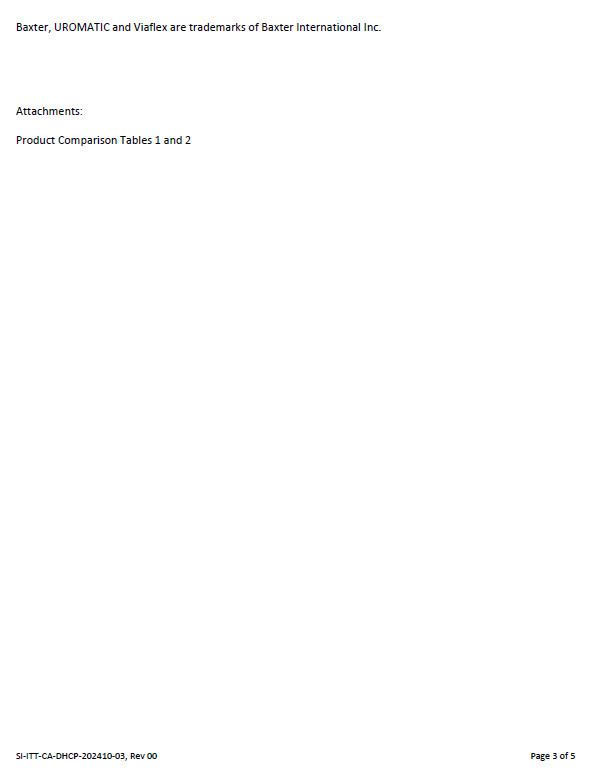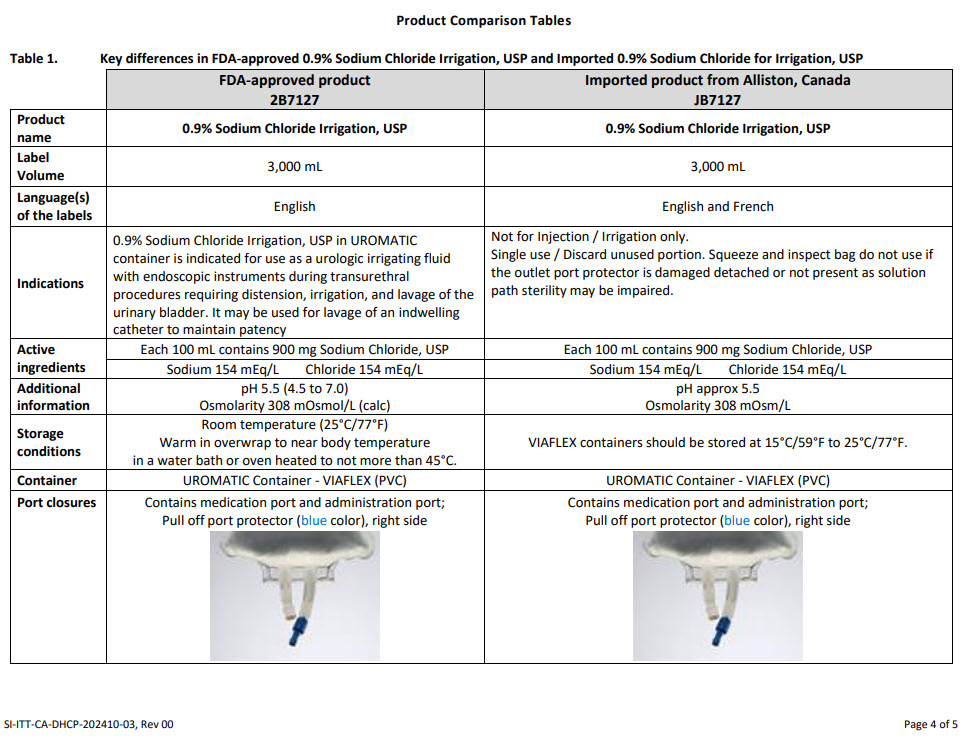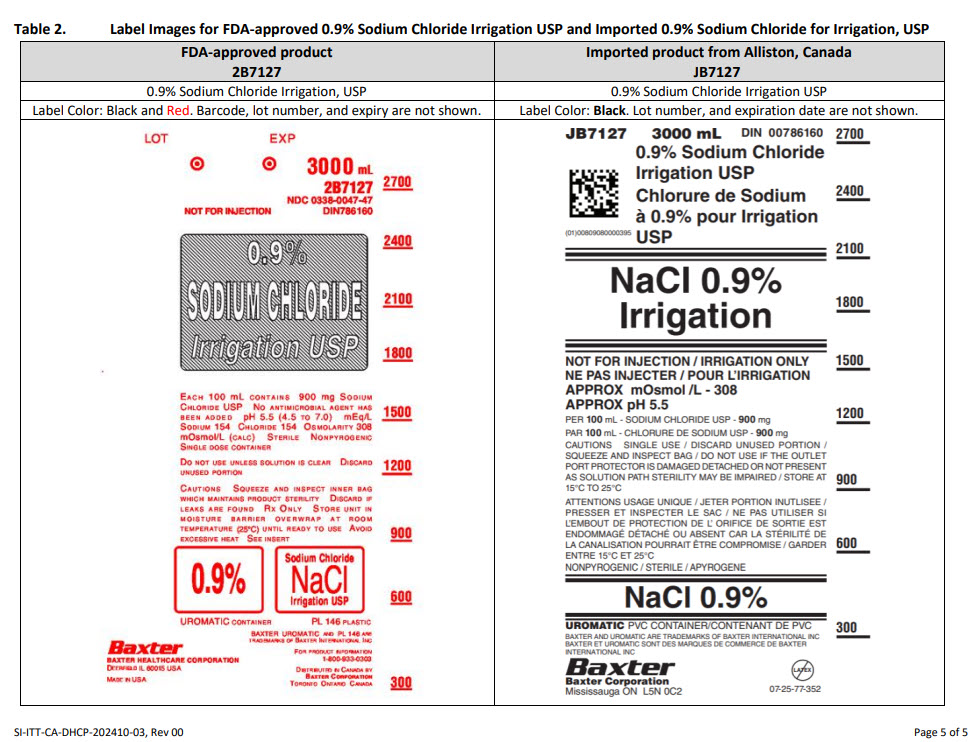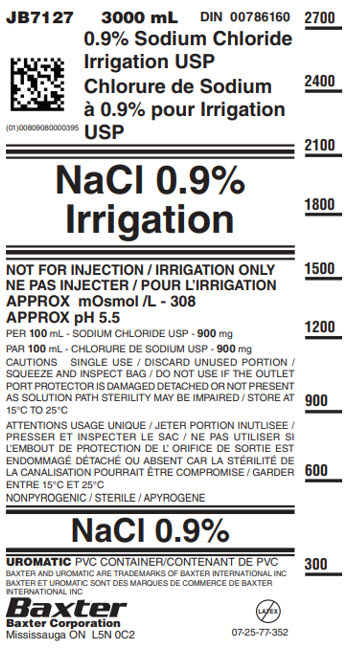 DRUG LABEL: Sodium Chloride
NDC: 0338-9834 | Form: IRRIGANT
Manufacturer: Baxter Healthcare Company
Category: prescription | Type: HUMAN PRESCRIPTION DRUG LABEL
Date: 20241203

ACTIVE INGREDIENTS: SODIUM CHLORIDE 900 mg/100 mL

0.9% Sodium chloride irrigation, usp

Health Care Professional Letter

Please refer to the FDA-approved prescribing information for the drug product listed below:

- 0.9% Sodium Chloride Irrigation, USP (click https://dailymed.nlm.nih.gov/dailymed/drugInfo.cfm?setid=886f889b-f3cf-4197-b307-6cfa88c89436)

Reporting Adverse Events or Product Quality Issues

To report adverse events associated with these imported products, please call Baxter at 1-866-888-2472, or fax: 1-800-759-1801. Adverse events or quality problems experienced with the use of these imported products may also be reported to the FDA’s MedWatch Adverse Event Reporting program either online, by regular mail or by fax:

- Complete and submit the report Online: https://www.fda.gov/safety/medwatch-fda-safety-information-and-adverse-event-reporting-program
- Regular mail or Fax: Download form https://www.fda.gov/safety/medwatch-fda-safety-information-and-adverse-event-reporting-program or call 1-800-332-1088 to request a reporting form, then complete and return to the address on the pre-addressed form, or submit by fax to 1-800-FDA-0178 (1-800-332-0178).

To report product quality issues associated with these imported products, please contact Baxter Product Surveillance through Baxter Product Feedback Portal (https://productfeedback.baxter.com/).

PACKAGE/LABEL PRINCIPAL DISPLAY PANEL

JB7127
3000 mL
DIN 00786160

0.9% Sodium Chloride
Irrigation USP

Chlorure de Sodium
à 0.9% pour Irrigation
USP

2D Barcode
(01)00809080000395

NaCl 0.9%
Irrigation

NOT FOR INJECTION / IRRIGATION ONLY
NE PAS INJECTER / POUR L’IRRIGATION
APPROX mOsmol /L – 308
APPROX pH 5.5

PER 100 mL – SODIUM CHLORIDE USP – 900 mg

PER 100 mL – CHLORURE DE SODIUM USP - 900 mg

CAUTIONS SINGLE USE / DISCARD UNUSED PORTION /
SQUEEZE AND INSPECT BAG / DO NOT USE IF THE OUTLET
PORT PROTECTOR IS DAMAGED DETACHED OR NOT PRESENT
AS SOLUTION PATH STERILITY MAY BE IMPAIRED / STORE AT
15°C TO 25°C

ATTENTIONS USAGE UNIQUE / JETER PORTION INUTILISEE /
PRESSER ET INSPECTER LE SAC / NE PAS UTILISER SI
L’EMBOUT DE PROTECTION DE L’ORIFICE DE SORTIE EST
ENDOMMAGÉ DÉTACHÉ OU ABSENT CAR LA STÉRILITÉ DE
LA CANALISATION POURRAIT ÊTRE COMPROMISE / GARDER
ENTRE 15°C TO 25°C

NONPYROGENIC / STERILE / APYROGENE

NaCl 0.9%

UROMATIC PVC CONTAINER/CONTENANT DE PVC

BAXTER AND UROMATIC ARE TRADEMARKS OF BAXTER INTERNATIONAL INC
BAXTER ET UROMATIC SONT DES MARQUES DE COMMERCE DE BAXTER
INTERNATIONAL INC.

Baxter Logo
Baxter Corporation
Mississauga ON L5N 0C2

No Latex Label
07-25-77-352

2700

2400

2100

1800

1500

1200

900

600

300